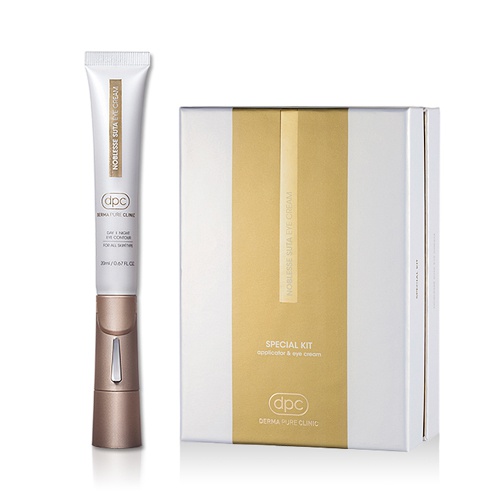 DRUG LABEL: DPC Noblesse Suta Eye
NDC: 71673-0004 | Form: CREAM
Manufacturer: MSCO
Category: otc | Type: HUMAN OTC DRUG LABEL
Date: 20170818

ACTIVE INGREDIENTS: ADENOSINE 0.04 g/100 mL; NIACINAMIDE 2 g/100 mL
INACTIVE INGREDIENTS: WATER; GLYCERIN

Drug Facts

ACTIVE INGREDIENT

Niacinamide, Adenosine

INACTIVE INGREDIENT

Water
Glycerin
Butylene Glycol
Hydrogenated Polydecene
Cyclopentasiloxane
Cyclohexasiloxane
1,2-Hexanediol
Butyrospermum Parkii (Shea) Butter
Dimethicone
Polysorbate 60
Hydrogenated Polyisobutene
Jojoba Esters
Polyacrylate-13
Cetearyl Olivate
Sorbitan Olivate
Cetearyl Alcohol
Cetearyl Glucoside
Cetyl Alcohol
Glyceryl Stearate
Phytosteryl/Isostearyl/Cetyl/Stearyl/Behenyl Dimer Dilinoleate
Polyisobutene
Caprylyl Glycol
Phenoxyethanol
Sodium Polyacrylate
Dimethicone Crosspolymer
Fragrance(Parfum)
Polysorbate 20
Sorbitan Isostearate
Dipotassium Glycyrrhizate
Ethylhexylglycerin
Disodium EDTA
Hydroxypropyl Starch Phosphate
Coccinia Indica Fruit Extract
Eclipta Prostrata Extract
Dextrin
Theobroma Cacao (Cocoa) Extract
Propanediol
Euterpe Oleracea Fruit Extract
Hippophae Rhamnoides Fruit Extract
Rubus Idaeus (Raspberry) Fruit Extract
Dipeptide Diaminobutyroyl Benzylamide Diacetate
Tocopherol
Anemarrhena Asphodeloides Root Extract
Croton Lechleri Resin Extract
Combretum Farinosum Flower Nectar
Acetyl Hexapeptide-8

PURPOSE

Skin Protectant - Whitening & Anti-wrinkle

keep out of reach of the children

INDICATIONS AND USAGE

Apply a proper amount on the skin and spread evenly.

WARNINGS

For external use only.
Avoid contact with eyes. Not for human consumption.
Discontinue use if irritation occurs.
If irritation persists, consult a physician.

DOSAGE AND ADMINISTRATION

for external use only